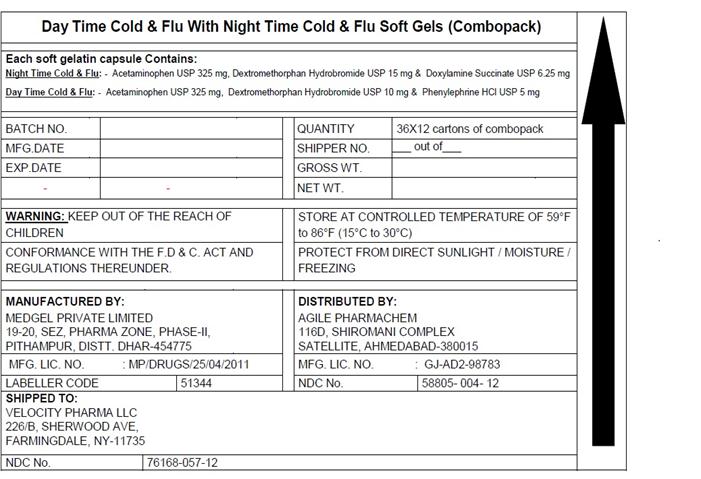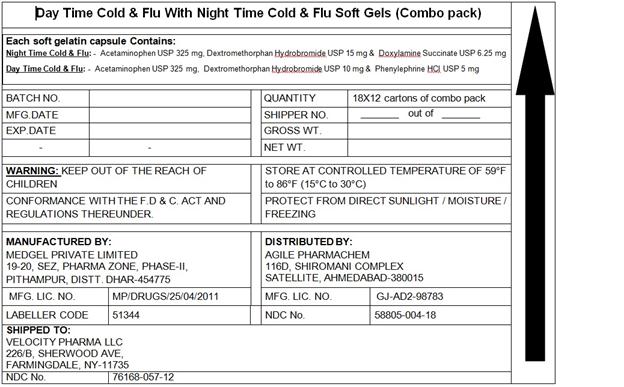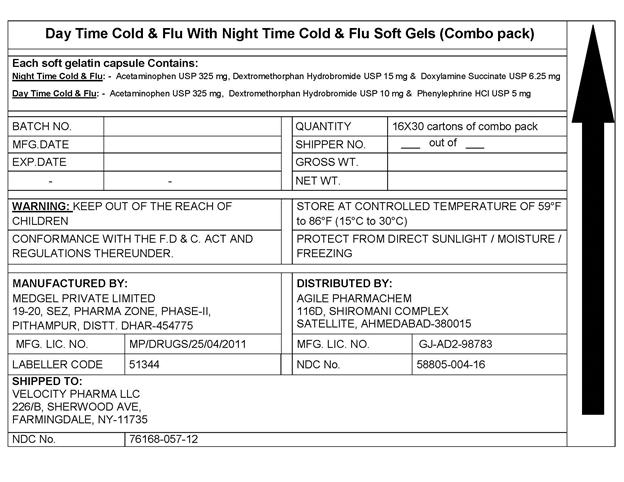 DRUG LABEL: DAYTIME NIGHTTIME COLD/FLU
NDC: 58805-004 | Form: KIT | Route: ORAL
Manufacturer: AGILE PHARMACHEM
Category: otc | Type: HUMAN OTC DRUG LABEL
Date: 20170920

ACTIVE INGREDIENTS: ACETAMINOPHEN 325 mg/1 1; DEXTROMETHORPHAN HYDROBROMIDE 10 mg/1 1; PHENYLEPHRINE HYDROCHLORIDE 5 mg/1 1; ACETAMINOPHEN 325 mg/1 1; DEXTROMETHORPHAN HYDROBROMIDE 15 mg/1 1; DOXYLAMINE SUCCINATE 6.25 mg/1 1
INACTIVE INGREDIENTS: FD&C RED NO. 40; FD&C YELLOW NO. 6; GELATIN; POLYETHYLENE GLYCOL 1000; POVIDONE; PROPYLENE GLYCOL; SORBITOL; TITANIUM DIOXIDE; FD&C BLUE NO. 1; FD&C YELLOW NO. 6; GELATIN; POLYETHYLENE GLYCOL 1000; POVIDONE; PROPYLENE GLYCOL; SORBITOL; TITANIUM DIOXIDE; GLYCERIN

Acetaminophen, Dextromethorphan and Phenylephrine Day time Cold and Flu

Active Ingredient

(in each softgel) of daytime cold and flu

Acetaminophen 325 mg

Dextromethorphan HBr 10 mg

Phenylephrine HCl 5 mg

(in each softgel) of nighttime cold and flu

Acetaminophen 325 mg

Dextromethorphan HBr 15 mg

Doxylamine Succinate 6.25 mg

Purpose

Daytime Cold and Flu:

pain reliever

Cough Suppressant

Nasal decongestant

Nighttime cold and flu purpose:

pain reliever

Cough Suppressant

Antihistamine

Uses

Daytime cold and flu: pain reliever, cough suppressant and Nasal decongestant

NightTime Cold and Flu: pain reliever, cough suppressant and Antihistamine

Warnings

Warnings Failure to follow these warnings could result in serious consequences.

Liver Warning: This product contains acetaminophen. Severe liver damage may occur if you take

- more than 4 doses in 24 hours which is maximum daily amount for this product
- with other drugs containing acetaminophen
- 3 or more alcoholic drinks daily while using this product
  do not use:
- with any other drug containing acetaminophen (prescription or not prescription). If you are not sure whether a drug contains acetaminophen, ask a doctor or pharmacist.
- if you are now taking a prescription monoamine oxidase inhibitor (MAOI) (Certain drugs for depression, psychiatric or emotional conditions or Parkinson’s disease), or for 2 weeks after stopping the MAOI drug, If you do not know if your prescription drug contains an MAOI, ask a doctor or pharmacist before taking this product.
  Ask a doctor before use if you have
- liver disease
- Heart disease
- Thyroid disease
- Diabetes
- High blood pressure
- Trouble urinating due to enlarged prostate gland
  ask your doctor or pharmacist before use if you are taking the blood thinning drug warfarin. When using this product, do not use more than directed.
  Stop use and ask a doctor if:
- Redness or swelling is present
- You get nervous, dizzy or sleepless
- Fever gets worse or lasts more than 3 days
- New symptoms occur
- Symptoms do not get better within 7 days or are accompanied by a fever
  NightTime Cold and Flu: Warnings Failure to follow these warnings could result in serious consequences.
  Liver Warning: This product contains acetaminophen. Severe liver damage may occur if you take
- more than 4 doses in 24 hours which is maximum daily amount for this product
- with other drugs containing acetaminophen
- 3 or more alcoholic drinks daily while using this product

do not use:

- with any other drug containing acetaminophen (prescription or not prescription). If you are not sure whether a drug contains acetaminophen, ask a doctor or pharmacist.
- if you are now taking a prescription monoamine oxidase inhibitor (MAOI) (Certain drugs for depression, psychiatric or emotional conditions or Parkinson’s disease), or for 2 weeks after stopping the MAOI drug, If you do not know if your prescription drug contains an MAOI, ask a doctor or pharmacist before taking this product.

Ask a doctor before use if you have

- liver disease
- Heart disease
- Thyroid disease
- Diabetes
- High blood pressure
- Trouble urinating due to enlarged prostate gland

- ask your doctor or pharmacist before use if you are taking the blood thinning drug warfarin. When using this product, do not use more than directed.
- Stop use and ask a doctor if:

- Redness or swelling is present
- You get nervous, dizzy or sleepless
- Fever gets worse or lasts more than 3 days
- New symptoms occur
- Symptoms do not get better within 7 days or are accompanied by a fever

If pregnant or breast-feeding, ask a health professional before use.

Overdose warning: Taking more than recommended dose (overdose) may cause liver damage. In case of overdose, get medical help or contact a Poison Control Center right away. Prompt medical attention is critical for adults as well as for children even if you do not notice any signs or symptoms.

Tamper evident: this package is safety sealed and child resistant. Use only if blisters are intact. If difficult to open use scissors.

Keep out of reach of children.

If pregnant or breast-feeding, ask a health professional before use.

Overdose warning: Taking more than recommended dose (overdose) may cause liver damage. In case of overdose, get medical help or contact a Poison Control Center right away. Prompt medical attention is critical for adults as well as for children even if you do not notice any signs or symptoms.

Tamper evident: this package is safety sealed and child resistant. Use only if blisters are intact. If difficult to open use scissors.

Direction

Daytime Cold and Flu:

- do not exceed 4 doses per 24 hours
- take only as directed – see overdose warning
- Adults and children 12 years and over: 2 softgels with water every 4 hours
- children under 12 years: ask a doctor
- Children under 4 years: do not use
  NightTime Cold and Flu
- do not exceed 4 doses per 24 hours
- take only as directed – see overdose warning
- Adults and children 12 years and over: 2 softgels with water every 4 hours
- children under 12 years: ask a doctor
- Children under 4 years: do not use

Other Information

- store at controlled temperature of 59°F to 86°F(15°C to 30°C)
- Protect from direct sun light /Moisture/Freezing

Inactive Ingredients

Daytime:

FD&C Red No.40, FD&C Yellow No. 6, Gelatin, Glycerin, Poyethylene Glycol, Povidone, Propylene Glycol, Purified Water, Sorbitol Special, Titanium dioxide

NightTime:

FD&C Blue No.1, FD&C Yellow No. 6, Gelatin, Glycerin, Poyethylene Glycol, Povidone, Propylene Glycol, Purified Water, Sorbitol Special, Titanium dioxide, glycerin

Questions or Comments

Call toll free 1-855-314-1850

PACKAGE LABEL.PRINCIPAL DISPLAY PANEL

NDC: 58805-004-12 12 softgels, 8 DayTime Cold and Flu, 4 NightTime Cold and Flu

NDC: 58805-004-16 12 softgels, 8 DayTime Cold and Flu, 4 NightTime Cold and Flu

NDC: 58805-004-18 12 softgels, 8 DayTime Cold and Flu, 4 NightTime Cold and Flu